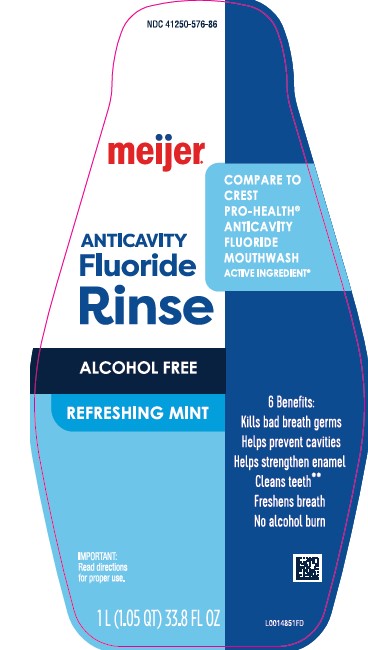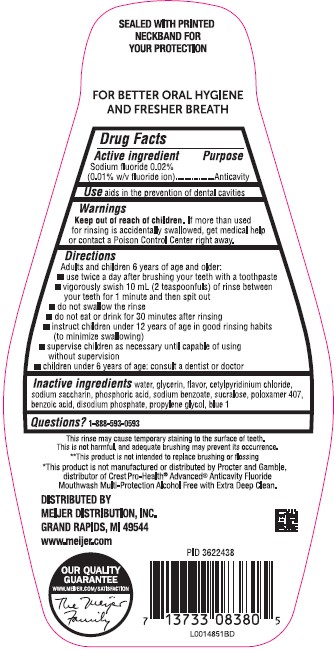 DRUG LABEL: Oral Antivavity
NDC: 41250-576 | Form: MOUTHWASH
Manufacturer: Meijer, Inc.
Category: otc | Type: HUMAN OTC DRUG LABEL
Date: 20260219

ACTIVE INGREDIENTS: SODIUM FLUORIDE 0.1 mg/1 mL
INACTIVE INGREDIENTS: WATER; GLYCERIN; SACCHARIN SODIUM; PHOSPHORIC ACID; SODIUM BENZOATE; SUCRALOSE; POLOXAMER 407; BENZOIC ACID; SODIUM PHOSPHATE, DIBASIC, ANHYDROUS; PROPYLENE GLYCOL; FD&C BLUE NO. 1; CETYLPYRIDINIUM CHLORIDE

Meijer 576.001/576AC-AD
Alcohol Free Fluoride Refreshing Mint Mouthwash

Tamper Evident Statement

SEALED WITH PRINTED NECKBAND FOR YOUR PROTECTION

Claims

FOR BETTER ORAL HYGIENE AND FRESHER BREATH

Active ingredient

Sodium fluoride 0.02% (0.01% w/v fluoride ion)

Purpose

Anticavity

Use

aids in the prevention of dental cavities

Warnings

For this product

Keep out of reach of children.

If more than used for rinsing is accidentally swallowed, get medical help or contact a Poison Control Center right away.

Directions

Adults and children 6 years of age and older:

- use twice a day after brushing your teeth with a toothpaste
- vigorously swish 10 mL (2 teaspoonfuls) of rinse bwtween your teeth for 1 minute then spit out
- do not swallow the rinse
- do not eat or drink for 30 minutes after rinsing
- instruct children under 12 years of age in good rinsing habits (to minimize swallowing)
- supervise children as necessary until capable of using witout supervision
- children under 6 years of age: consult a dentist or doctor

Inactive ingredients

water, glycerin, flavor, cetylpyridinium chloride, sodium saccharin, phosphoric acid, sodium benzoate, sucralose, poloxamer 407, benzoic acid, disodium phosphate, propylene glycol, blue 1

Questions?

1-888-593-0593

Disclaimer

This rinse may cause temporary staining to the surface of teeth. This is not harmful, and adequate brushing may prevent its occurrence.

**This product is not intended to replace brushing or flossing.

*This product is not manufactured or distributed by Procter and Gamble, distributor of Crest Pro-Health® Advanced® Anticavity Fluoride Mouthwash Multi-Protection Alcohol Free with Extra Deep Clean.

Adverse Reactions

DISTRIBUTED BY

MEIJER DISTRIBUTION, INC.

GRAND RAPIDS, MI 49544

www.meijer.com

OUR QUALITY GUARANTEE

WWW.MEIJER.COM/SATISFACTION

The Meijer Family

Principal display panel

NDC 41250-576-86

meijer®

Compare to Crest Pro-Health® ANTICAVITY FLUORIDE MOUTHWASH ACTIVE INGREDIENT*

ANTICAVITY

Fluoride Rinse

ALCOHOL FREE

REFRESHING MINT

6 Benefits:

Kills bad breath germs

Helps prevent cavities

Helps strengthen enamel

Cleans teeth**

Freshen breath

No alcohol burn

IMPORTANT: Read directions for proper use.

1L (1.05 QT) 33.8 FL OZ